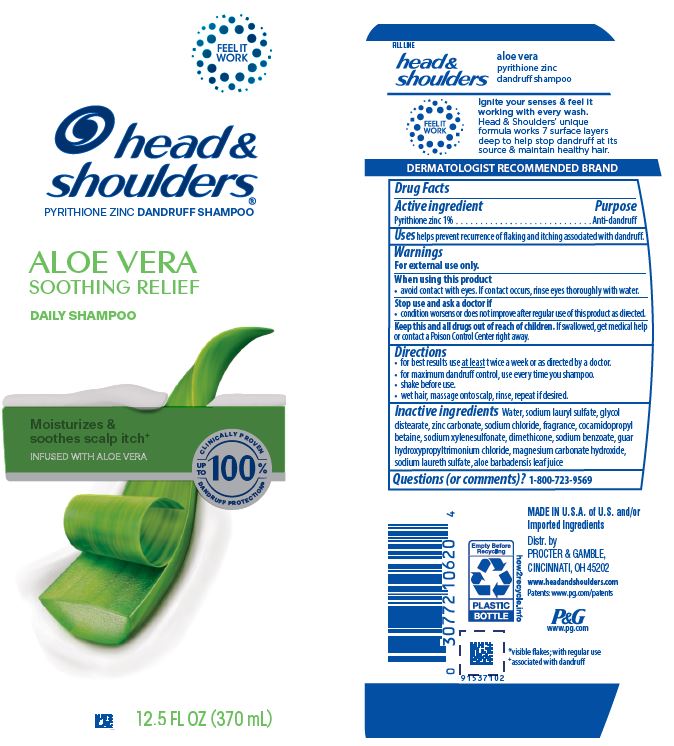 DRUG LABEL: Head and Shoulders Aloe Vera Soothing Relief Daily
NDC: 84126-053 | Form: SHAMPOO
Manufacturer: The Procter & Gamble Manufacturing Company
Category: otc | Type: HUMAN OTC DRUG LABEL
Date: 20251231

ACTIVE INGREDIENTS: PYRITHIONE ZINC 1 g/100 mL
INACTIVE INGREDIENTS: SODIUM LAURETH SULFATE; WATER; ZINC CARBONATE; SODIUM CHLORIDE; SODIUM XYLENESULFONATE; COCAMIDOPROPYL BETAINE; GLYCOL DISTEARATE; GUAR HYDROXYPROPYLTRIMONIUM CHLORIDE; ALOE BARBADENSIS LEAF JUICE; DIMETHICONE; MAGNESIUM CARBONATE HYDROXIDE; SODIUM BENZOATE; SODIUM LAURYL SULFATE

Head and Shoulders® Aloe Vera Soothing Relief Daily Shampoo

Drug Facts

Active ingredient

Pyrithione zinc 1%

Purpose

Anti-dandruff

Uses

helps prevent recurrence of flaking and itching associated with dandruff.

Warnings

For external use only.

When using this product

- avoid contact with eyes. If contact occurs, rinse eyes thoroughly with water.

Stop use and ask a doctor if

- condition worsens or does not improve after regular use of this product as directed.

KEEP OUT OF REACH OF CHILDREN

Keep this and all drugs out of reach of children. If swallowed, get medical help or contact a Poison Control Center right away.

Directions

- for best results use at least twice a week or as directed by a doctor.
- for maximum dandruff control, use every time you shampoo.
- shake before use.
- wet hair, massage onto scalp, rinse, repeat if desired.

Inactive Ingredients

Water, sodium lauryl sulfate, glycol distearate, zinc carbonate, sodium chloride, fragrance, cocamidopropyl betaine, sodium xylenesulfonate, dimethicone, sodium benzoate, guar hydroxypropyltrimonium chloride, magnesium carbonate hydroxide, sodium laureth sulfate, aloe barbadensis leaf juice

Questions (or comments)?

1-800-723-9569

Dist. by PROCTER & GAMBLE,
CINCINNATI, OH 45202

PRINCIPAL DISPLAY PANEL - 370 mL Bottle Label

head &
shoulders®
PYRITHIONE ZINC DANDRUFF SHAMPOO

ALOE VERA

SOOTHING RELIEF

DAILY SHAMPOO

12.5 FL OZ (370 mL)